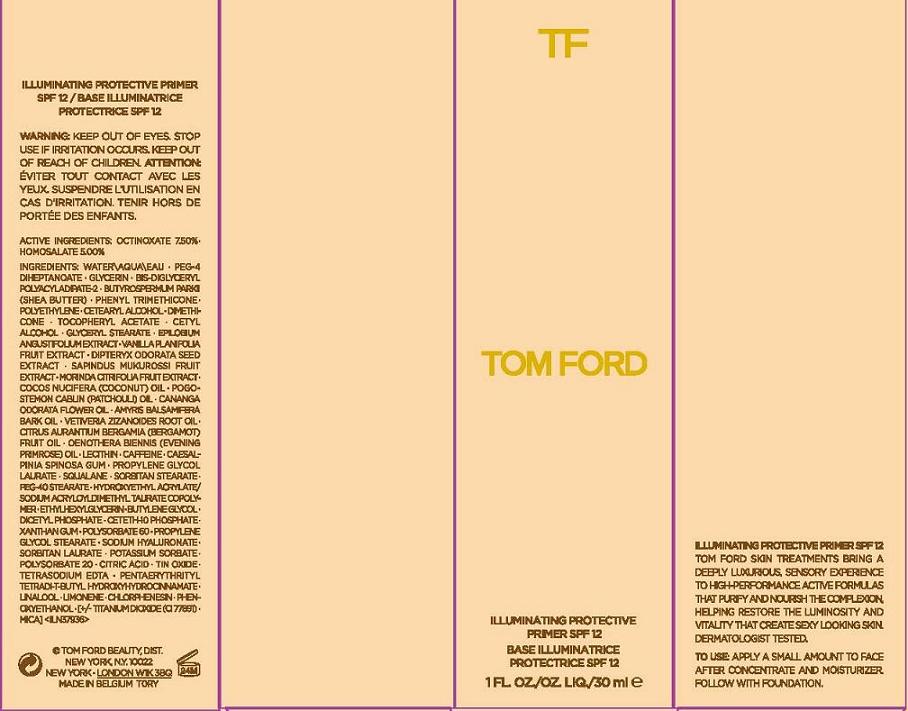 DRUG LABEL: ILLUMINATING PROTECTIVE PRIMER
NDC: 76398-001 | Form: CREAM
Manufacturer: TOM FORD BEAUTY DIST
Category: otc | Type: HUMAN OTC DRUG LABEL
Date: 20111020

ACTIVE INGREDIENTS: OCTINOXATE 7.5 mL/100 mL; HOMOSALATE 5.0 mL/100 mL
INACTIVE INGREDIENTS: WATER; GLYCERIN; SHEA BUTTER; PHENYL TRIMETHICONE; CETOSTEARYL ALCOHOL; DIMETHICONE; ALPHA-TOCOPHEROL ACETATE; CETYL ALCOHOL; GLYCERYL MONOSTEARATE; EPILOBIUM ANGUSTIFOLIUM LEAF; VANILLA; DIPTERYX ODORATA SEED; SAPINDUS MUKOROSSI FRUIT; COCONUT OIL; PATCHOULI OIL; CANANGA OIL; AMYRIS BALSAMIFERA OIL; VETIVER OIL; BERGAMOT OIL; EVENING PRIMROSE OIL; LECITHIN, SOYBEAN; CAFFEINE; CAESALPINIA SPINOSA RESIN; PROPYLENE GLYCOL LAURATES; SQUALANE; SORBITAN MONOSTEARATE; PEG-40 STEARATE; ETHYLHEXYLGLYCERIN; BUTYLENE GLYCOL; DIHEXADECYL PHOSPHATE; CETETH-10 PHOSPHATE; XANTHAN GUM; POLYSORBATE 60; HYALURONATE SODIUM; SORBITAN MONOLAURATE; POTASSIUM SORBATE; POLYSORBATE 20; CITRIC ACID MONOHYDRATE; STANNIC OXIDE; EDETATE SODIUM; CHLORPHENESIN; PHENOXYETHANOL; TITANIUM DIOXIDE; MICA

ACTIVE INGREDIENTS: OCTINOXATE 7.50% [] HOMOSALATE 5.00%

INACTIVE INGREDIENT

INGREDIENTS: WATER\AQUA\EAU [] PEG-4 DIHEPTANOATE [] GLYCERIN [] BIS-DIGLYCERYL POLYACYLADIPATE-2 [] BUTYROSPERMUM PARKII (SHEA BUTTER) [] PHENYL TRIMETHICONE [] POLYETHYLENE [] CETEARYL ALCOHOL [] DIMETHICONE [] TOCOPHERYL ACETATE [] CETYL ALCOHOL [] GLYCERYL STEARATE [] EPILOBIUM ANGUSTIFOLIUM EXTRACT [] VANILLA PLANIFOLIA FRUIT EXTRACT [] DIPTERYX ODORATA SEED EXTRACT [] SAPINDUS MUKUROSSI FRUIT EXTRACT [] MORINDA CITRIFOLIA FRUIT EXTRACT [] COCOS NUCIFERA (COCONUT) OIL [] POGOSTEMON CABLIN (PATCHOULI) OIL [] CANANGA ODORATA FLOWER OIL [] AMYRIS BALSAMIFERA BARK OIL [] VETIVERIA ZIZANOIDES ROOT OIL [] CITRUS AURANTIUM BERGAMIA (BERGAMOT) FRUIT OIL [] OENOTHERA BIENNIS (EVENING PRIMROSE) OIL [] LECITHIN [] CAFFEINE [] CAESALPINIA SPINOSA GUM [] PROPYLENE GLYCOL LAURATE [] SQUALANE [] SORBITAN STEARATE [] PEG-40 STEARATE [] HYDROXYETHYL ACRYLATE/SODIUM ACRYLOYLDIMETHYL TAURATE COPOLYMER [] ETHYLHEXYLGLYCERIN [] BUTYLENE GLYCOL [] DICETYL PHOSPHATE [] CETETH-10 PHOSPHATE [] XANTHAN GUM [] POLYSORBATE 60 [] PROPYLENE GLYCOL STEARATE [] SODIUM HYALURONATE [] SORBITAN LAURATE [] POTASSIUM SORBATE [] POLYSORBATE 20 [] CITRIC ACID [] TIN OXIDE [] TETRASODIUM EDTA [] PENTAERYTHRITYL TETRA-DI-T-BUTYL HYDROXYHYDROCINNAMATE [] LINALOOL [] LIMONENE [] CHLORPHENESIN [] PHENOXYETHANOL [] [+/- TITANIUM DIOXIDE (CI 77891) [] MICA]

WARNINGS

WARNING: KEEP OUT OF EYES. STOP USE IF IRRITATION OCCURS. KEEP OUT OF REACH OF CHILDREN.

PACKAGE LABEL

PRINCIPAL DISPLAY PANEL:

TF

TOM FORD

ILLUMINATING PROTECTIVE PRIMER SPF 12

1 OZ./FL.OZ./30 ML

TOM FORD BEAUTY DIST

NEW YORK, NY 10022